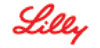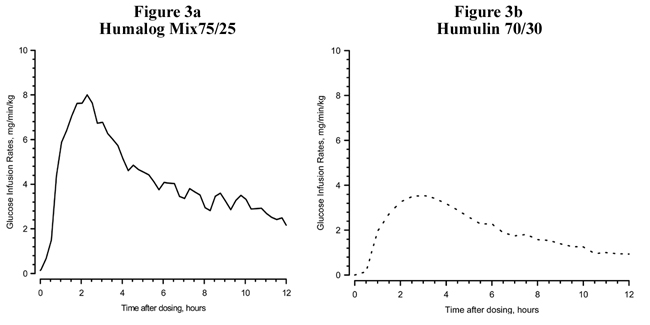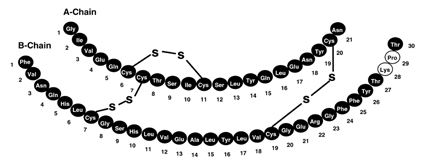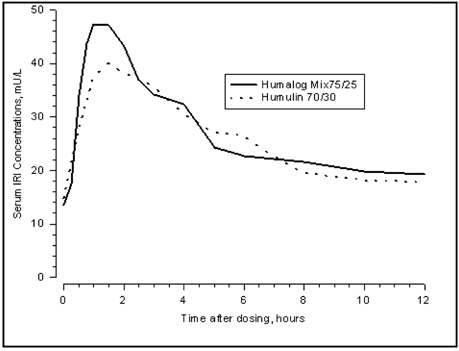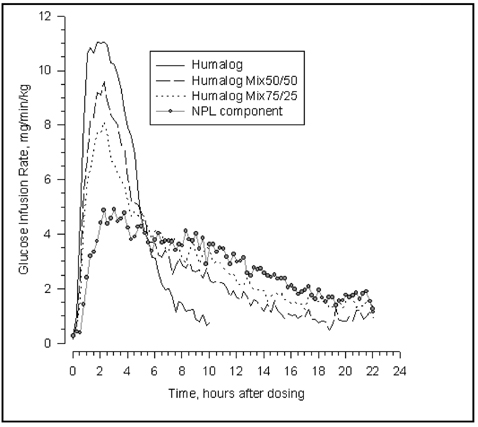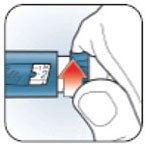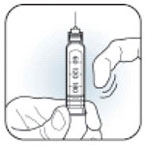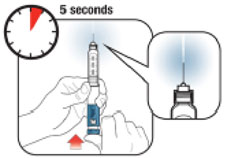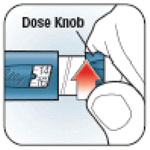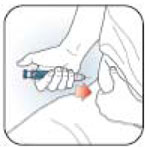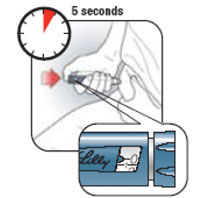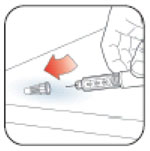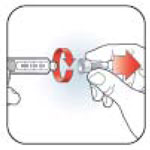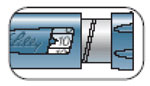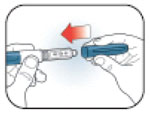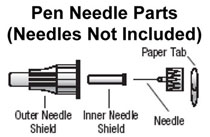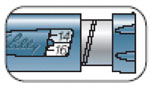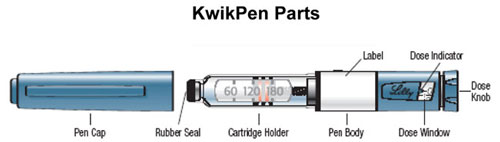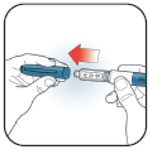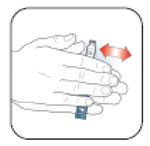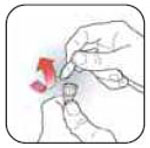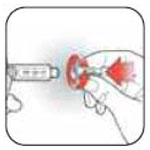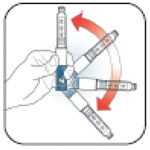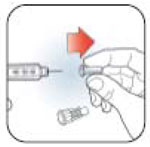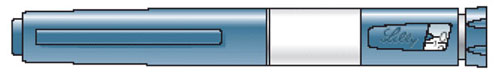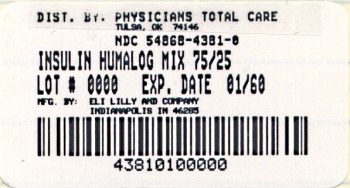 DRUG LABEL: Humalog
NDC: 54868-4381 | Form: INJECTION, SUSPENSION
Manufacturer: Physicians Total Care, Inc.
Category: prescription | Type: Human prescription drug label
Date: 20111220

ACTIVE INGREDIENTS: Insulin lispro 100 [iU]/1 mL
INACTIVE INGREDIENTS: Protamine sulfate 0.28 mg/1 mL; Glycerin 16 mg/1 mL; sodium phosphate, dibasic 3.78 mg/1 mL; Metacresol 1.76 mg/1 mL; Zinc .025 mg/1 mL; Phenol .715 mg/1 mL; Water; Hydrochloric acid; Sodium hydroxide

HUMALOG® Mix75/25TM
75% INSULIN LISPRO PROTAMINE SUSPENSION AND
25% INSULIN LISPRO INJECTION
(rDNA ORIGIN)
100 UNITS PER ML (U-100)

DESCRIPTION

Humalog® Mix75/25™ [75% insulin lispro protamine suspension and 25% insulin lispro injection, (rDNA origin)] is a mixture of insulin lispro solution, a rapid–acting blood glucose–lowering agent and insulin lispro protamine suspension, an intermediate–acting blood glucose–lowering agent. Chemically, insulin lispro is Lys(B28), Pro(B29) human insulin analog, created when the amino acids at positions 28 and 29 on the insulin B–chain are reversed. Insulin lispro is synthesized in a special non–pathogenic laboratory strain of Escherichia coli bacteria that has been genetically altered to produce insulin lispro. Insulin lispro protamine suspension (NPL component) is a suspension of crystals produced from combining insulin lispro and protamine sulfate under appropriate conditions for crystal formation.

Insulin lispro has the following primary structure:

Insulin lispro has the empirical formula C257H383N65O77S6 and a molecular weight of 5808, both identical to that of human insulin.

Humalog Mix75/25 vials and Pens contain a sterile suspension of insulin lispro protamine suspension mixed with soluble insulin lispro for use as an injection.

Each milliliter of Humalog Mix75/25 injection contains insulin lispro 100 units, 0.28 mg protamine sulfate, 16 mg glycerin, 3.78 mg dibasic sodium phosphate, 1.76 mg Metacresol, zinc oxide content adjusted to provide 0.025 mg zinc ion, 0.715 mg phenol, and Water for Injection. Humalog Mix75/25 has a pH of 7.0 to 7.8. Hydrochloric acid 10% and/or sodium hydroxide 10% may have been added to adjust pH.

CLINICAL PHARMACOLOGY

Antidiabetic Activity

The primary activity of insulin, including Humalog Mix75/25, is the regulation of glucose metabolism. In addition, all insulins have several anabolic and anti–catabolic actions on many tissues in the body. In muscle and other tissues (except the brain), insulin causes rapid transport of glucose and amino acids intracellularly, promotes anabolism, and inhibits protein catabolism. In the liver, insulin promotes the uptake and storage of glucose in the form of glycogen, inhibits gluconeogenesis, and promotes the conversion of excess glucose into fat.

Insulin lispro, the rapid–acting component of Humalog Mix75/25, has been shown to be equipotent to Regular human insulin on a molar basis. One unit of Humalog® has the same glucose–lowering effect as one unit of Regular human insulin, but its effect is more rapid and of shorter duration. Humalog Mix75/25 has a similar glucose–lowering effect as compared with Humulin® 70/30 on a unit for unit basis.

Pharmacokinetics

Absorption

Studies in nondiabetic subjects and patients with type 1 (insulin–dependent) diabetes demonstrated that Humalog, the rapid–acting component of Humalog Mix75/25, is absorbed faster than Regular human insulin (U–100). In nondiabetic subjects given subcutaneous doses of Humalog ranging from 0.1 to 0.4 U/kg, peak serum concentrations were observed 30 to 90 minutes after dosing. When nondiabetic subjects received equivalent doses of Regular human insulin, peak insulin concentrations occurred between 50 to 120 minutes after dosing. Similar results were seen in patients with type 1 diabetes.

Figure 1: Serum Immunoreactive Insulin (IRI) Concentrations, After Subcutaneous Injection of Humalog Mix75/25 or Humulin 70/30 in Healthy Nondiabetic Subjects.

Humalog Mix75/25 has two phases of absorption. The early phase represents insulin lispro and its distinct characteristics of rapid onset. The late phase represents the prolonged action of insulin lispro protamine suspension. In 30 healthy nondiabetic subjects given subcutaneous doses (0.3 U/kg) of Humalog Mix75/25, peak serum concentrations were observed 30 to 240 minutes (median, 60 minutes) after dosing (see Figure 1). Identical results were found in patients with type 1 diabetes. The rapid absorption characteristics of Humalog are maintained with Humalog Mix75/25 (see Figure 1).

Figure 1 represents serum insulin concentration versus time curves of Humalog Mix75/25 and Humulin 70/30. Humalog Mix75/25 has a more rapid absorption than Humulin 70/30, which has been confirmed in patients with type 1 diabetes.

Distribution

Radiolabeled distribution studies of Humalog Mix75/25 have not been conducted. However, the volume of distribution following injection of Humalog is identical to that of Regular human insulin, with a range of 0.26 to 0.36 L/kg.

Metabolism

Human metabolism studies of Humalog Mix75/25 have not been conducted. Studies in animals indicate that the metabolism of Humalog, the rapid–acting component of Humalog Mix75/25, is identical to that of Regular human insulin.

Elimination

Humalog Mix75/25 has two absorption phases, a rapid and a prolonged phase, representative of the insulin lispro and insulin lispro protamine suspension components of the mixture. As with other intermediate-acting insulins, a meaningful terminal phase half–life cannot be calculated after administration of Humalog Mix75/25 because of the prolonged insulin lispro protamine suspension absorption.

Pharmacodynamics

Studies in nondiabetic subjects and patients with diabetes demonstrated that Humalog has a more rapid onset of glucose–lowering activity, an earlier peak for glucose–lowering, and a shorter duration of glucose–lowering activity than Regular human insulin. The early onset of activity of Humalog Mix75/25 is directly related to the rapid absorption of Humalog. The time course of action of insulin and insulin analogs, such as Humalog (and hence Humalog Mix75/25), may vary considerably in different individuals or within the same individual. The parameters of Humalog Mix75/25 activity (time of onset, peak time, and duration) as presented in Figures 2 and 3 should be considered only as general guidelines. The rate of insulin absorption and consequently the onset of activity is known to be affected by the site of injection, exercise, and other variables (see General under PRECAUTIONS).

In a glucose clamp study performed in 30 nondiabetic subjects, the onset of action and glucose–lowering activity of Humalog, Humalog® Mix50/50™, Humalog Mix75/25, and insulin lispro protamine suspension (NPL component) were compared (see Figure 2). Graphs of mean glucose infusion rate versus time showed a distinct insulin activity profile for each formulation. The rapid onset of glucose–lowering activity characteristic of Humalog was maintained in Humalog Mix75/25.

In separate glucose clamp studies performed in nondiabetic subjects, pharmacodynamics of Humalog Mix75/25 and Humulin 70/30 were assessed and are presented in Figure 3. Humalog Mix75/25 has a duration of activity similar to that of Humulin 70/30.

Figure 2: Insulin Activity After Injection of Humalog, Humalog Mix50/50, Humalog Mix75/25, or Insulin Lispro Protamine Suspension (NPL Component) in 30 Nondiabetic Subjects.
Figure 3: Insulin Activity After Injection of Humalog Mix75/25 and Humulin 70/30 in Nondiabetic Subjects.

Figures 2 and 3 represent insulin activity profiles as measured by glucose clamp studies in healthy nondiabetic subjects.

Figure 2 shows the time activity profiles of Humalog, Humalog Mix50/50, Humalog Mix75/25, and insulin lispro protamine suspension (NPL component).

Figure 3 is a comparison of the time activity profiles of Humalog Mix75/25 (see Figure 3a) and of Humulin 70/30 (see Figure 3b) from two different studies.

Special Populations

Age and Gender

Information on the effect of age on the pharmacokinetics of Humalog Mix75/25 is unavailable. Pharmacokinetic and pharmacodynamic comparisons between men and women administered Humalog Mix75/25 showed no gender differences. In large Humalog clinical trials, sub-group analysis based on age and gender demonstrated that differences between Humalog and Regular human insulin in postprandial glucose parameters are maintained across sub-groups.

Smoking

The effect of smoking on the pharmacokinetics and pharmacodynamics of Humalog Mix75/25 has not been studied.

Pregnancy

The effect of pregnancy on the pharmacokinetics and pharmacodynamics of Humalog Mix75/25 has not been studied.

Obesity

The effect of obesity and/or subcutaneous fat thickness on the pharmacokinetics and pharmacodynamics of Humalog Mix75/25 has not been studied. In large clinical trials, which included patients with Body Mass Index up to and including 35 kg/m^2, no consistent differences were observed between Humalog and Humulin® R with respect to postprandial glucose parameters.

Renal Impairment

The effect of renal impairment on the pharmacokinetics and pharmacodynamics of Humalog Mix75/25 has not been studied. In a study of 25 patients with type 2 diabetes and a wide range of renal function, the pharmacokinetic differences between Humalog and Regular human insulin were generally maintained. However, the sensitivity of the patients to insulin did change, with an increased response to insulin as the renal function declined. Careful glucose monitoring and dose reductions of insulin, including Humalog Mix75/25, may be necessary in patients with renal dysfunction.

Hepatic Impairment

Some studies with human insulin have shown increased circulating levels of insulin in patients with hepatic failure. The effect of hepatic impairment on the pharmacokinetics and pharmacodynamics of Humalog Mix75/25 has not been studied. However, in a study of 22 patients with type 2 diabetes, impaired hepatic function did not affect the subcutaneous absorption or general disposition of Humalog when compared with patients with no history of hepatic dysfunction. In that study, Humalog maintained its more rapid absorption and elimination when compared with Regular human insulin. Careful glucose monitoring and dose adjustments of insulin, including Humalog Mix75/25, may be necessary in patients with hepatic dysfunction.

INDICATIONS AND USAGE

Humalog Mix75/25, a mixture of 75% insulin lispro protamine suspension and 25% insulin lispro injection, (rDNA origin), is indicated in the treatment of patients with diabetes mellitus for the control of hyperglycemia. Humalog Mix75/25 has a more rapid onset of glucose–lowering activity compared with Humulin 70/30 while having a similar duration of action. This profile is achieved by combining the rapid onset of Humalog with the intermediate action of insulin lispro protamine suspension.

CONTRAINDICATIONS

Humalog Mix75/25 is contraindicated during episodes of hypoglycemia and in patients sensitive to insulin lispro or any of the excipients contained in the formulation.

WARNINGS

Humalog differs from Regular human insulin by its rapid onset of action as well as a shorter duration of activity. Therefore, the dose of Humalog Mix75/25 should be given within 15 minutes before a meal.

Hypoglycemia is the most common adverse effect associated with the use of insulins, including Humalog Mix75/25. As with all insulins, the timing of hypoglycemia may differ among various insulin formulations. Glucose monitoring is recommended for all patients with diabetes.

Any change of insulin should be made cautiously and only under medical supervision. Changes in insulin strength, manufacturer, type (e.g., Regular, NPH, analog), species, or method of manufacture may result in the need for a change in dosage.

PRECAUTIONS

General

Hypoglycemia and hypokalemia are among the potential clinical adverse effects associated with the use of all insulins. Because of differences in the action of Humalog Mix75/25 and other insulins, care should be taken in patients in whom such potential side effects might be clinically relevant (e.g., patients who are fasting, have autonomic neuropathy, or are using potassium–lowering drugs or patients taking drugs sensitive to serum potassium level). Lipodystrophy and hypersensitivity are among other potential clinical adverse effects associated with the use of all insulins.

As with all insulin preparations, the time course of Humalog Mix75/25 action may vary in different individuals or at different times in the same individual and is dependent on site of injection, blood supply, temperature, and physical activity.

Adjustment of dosage of any insulin may be necessary if patients change their physical activity or their usual meal plan. Insulin requirements may be altered during illness, emotional disturbances, or other stress.

Hypoglycemia — As with all insulin preparations, hypoglycemic reactions may be associated with the administration of Humalog Mix75/25. Rapid changes in serum glucose concentrations may induce symptoms of hypoglycemia in persons with diabetes, regardless of the glucose value. Early warning symptoms of hypoglycemia may be different or less pronounced under certain conditions, such as long duration of diabetes, diabetic nerve disease, use of medications such as beta–blockers, or intensified diabetes control.

Renal Impairment — As with other insulins, the requirements for Humalog Mix75/25 may be reduced in patients with renal impairment.

Hepatic Impairment — Although impaired hepatic function does not affect the absorption or disposition of Humalog, careful glucose monitoring and dose adjustments of insulin, including Humalog Mix75/25, may be necessary.

Allergy — Local Allergy — As with any insulin therapy, patients may experience redness, swelling, or itching at the site of injection. These minor reactions usually resolve in a few days to a few weeks. In some instances, these reactions may be related to factors other than insulin, such as irritants in the skin cleansing agent or poor injection technique.

Systemic Allergy — Less common, but potentially more serious, is generalized allergy to insulin, which may cause rash (including pruritus) over the whole body, shortness of breath, wheezing, reduction in blood pressure, rapid pulse, or sweating. Severe cases of generalized allergy, including anaphylactic reaction, may be life threatening. Localized reactions and generalized myalgias have been reported with the use of cresol as an injectable excipient.

Antibody Production — In clinical trials, antibodies that cross-react with human insulin and insulin lispro were observed in both human insulin mixtures and insulin lispro mixtures treatment groups.

Information for Patients

Patients should be informed of the potential risks and advantages of Humalog Mix75/25 and alternative therapies. Patients should not mix Humalog Mix75/25 with any other insulin. They should also be informed about the importance of proper insulin storage, injection technique, timing of dosage, adherence to meal planning, regular physical activity, regular blood glucose monitoring, periodic hemoglobin A1c testing, recognition and management of hypo- and hyperglycemia, and periodic assessment for diabetes complications.

Patients should be advised to inform their physician if they are pregnant or intend to become pregnant.

Refer patients to the Patient Information leaflet for information on normal appearance, timing of dosing (within 15 minutes before a meal), storing, and common adverse effects.

For Patients Using Insulin Pen Delivery Devices: Before starting therapy, patients should read the Patient Information leaflet that accompanies the drug product and the User Manual that accompanies the delivery device and re-read them each time the prescription is renewed. Patients should be instructed on how to properly use the delivery device, prime the Pen to a stream of insulin, and properly dispose of needles. Patients should be advised not to share their Pens with others.

Laboratory Tests

As with all insulins, the therapeutic response to Humalog Mix75/25 should be monitored by periodic blood glucose tests. Periodic measurement of hemoglobin A1c is recommended for the monitoring of long–term glycemic control.

Drug Interactions

Insulin requirements may be increased by medications with hyperglycemic activity such as corticosteroids, isoniazid, certain lipid-lowering drugs (e.g., niacin), estrogens, oral contraceptives, phenothiazines, and thyroid replacement therapy.

Insulin requirements may be decreased in the presence of drugs that increase insulin sensitivity or have hypoglycemic activity, such as oral antidiabetic agents, salicylates, sulfa antibiotics, certain antidepressants (monoamine oxidase inhibitors), angiotensin-converting-enzyme inhibitors, angiotensin II receptor blocking agents, beta-adrenergic blockers, inhibitors of pancreatic function (e.g., octreotide), and alcohol. Beta–adrenergic blockers may mask the symptoms of hypoglycemia in some patients.

Carcinogenesis, Mutagenesis, Impairment of Fertility

Long-term studies in animals have not been performed to evaluate the carcinogenic potential of Humalog, Humalog Mix75/25, or Humalog Mix50/50. Insulin lispro was not mutagenic in a battery of in vitro and in vivo genetic toxicity assays (bacterial mutation tests, unscheduled DNA synthesis, mouse lymphoma assay, chromosomal aberration tests, and a micronucleus test). There is no evidence from animal studies of impairment of fertility induced by insulin lispro.

Pregnancy

Teratogenic Effects — Pregnancy Category B

Reproduction studies with insulin lispro have been performed in pregnant rats and rabbits at parenteral doses up to 4 and 0.3 times, respectively, the average human dose (40 units/day) based on body surface area. The results have revealed no evidence of impaired fertility or harm to the fetus due to insulin lispro. There are, however, no adequate and well–controlled studies with Humalog, Humalog Mix75/25, or Humalog Mix50/50 in pregnant women. Because animal reproduction studies are not always predictive of human response, this drug should be used during pregnancy only if clearly needed.

Nursing Mothers

It is unknown whether insulin lispro is excreted in significant amounts in human milk. Many drugs, including human insulin, are excreted in human milk. For this reason, caution should be exercised when Humalog Mix75/25 is administered to a nursing woman. Patients with diabetes who are lactating may require adjustments in Humalog Mix75/25 dose, meal plan, or both.

Pediatric Use

Safety and effectiveness of Humalog Mix75/25 in patients less than 18 years of age have not been established.

Geriatric Use

Clinical studies of Humalog Mix75/25 did not include sufficient numbers of patients aged 65 and over to determine whether they respond differently than younger patients. In general, dose selection for an elderly patient should take into consideration the greater frequency of decreased hepatic, renal, or cardiac function, and of concomitant disease or other drug therapy in this population.

ADVERSE REACTIONS

Clinical studies comparing Humalog Mix75/25 with human insulin mixtures did not demonstrate a difference in frequency of adverse events between the two treatments.

Adverse events commonly associated with human insulin therapy include the following:

Body as a Whole — allergic reactions (see PRECAUTIONS).

Skin and Appendages — injection site reaction, lipodystrophy, pruritus, rash.

Other — hypoglycemia (see WARNINGS and PRECAUTIONS).

OVERDOSAGE

Hypoglycemia may occur as a result of an excess of insulin relative to food intake, energy expenditure, or both. Mild episodes of hypoglycemia usually can be treated with oral glucose. Adjustments in drug dosage, meal patterns, or exercise, may be needed. More severe episodes with coma, seizure, or neurologic impairment may be treated with intramuscular/subcutaneous glucagon or concentrated intravenous glucose. Sustained carbohydrate intake and observation may be necessary because hypoglycemia may recur after apparent clinical recovery.

DOSAGE AND ADMINISTRATION

Table 1: Summary of Pharmacodynamic Properties of Insulin Products (Pooled Cross-Study Comparison)
Insulin Products | Dose, U/kg | Time of Peak Activity, Hours After Dosing | Percent of Total Activity Occurring in the First 4 Hours
Humalog | 0.3 | 2.4 (0.8 – 4.3) | 70% (49 – 89%)
Humulin R | 0.32 (0.26 – 0.37) | 4.4 (4.0 – 5.5) | 54% (38 – 65%)
Humalog Mix75/25 | 0.3 | 2.6 (1.0 – 6.5) | 35% (21 – 56%)
Humulin 70/30 | 0.3 | 4.4 (1.5 – 16) | 32% (14 – 60%)
Humalog Mix50/50 | 0.3 | 2.3 (0.8 – 4.8) | 45% (27 – 69%)
Humulin 50/50 | 0.3 | 3.3 (2.0 – 5.5) | 44% (21 – 60%)
NPH | 0.32 (0.27 – 0.40) | 5.5 (3.5 – 9.5) | 14% (3.0 – 48%)
NPL component | 0.3 | 5.8 (1.3 – 18.3) | 22% (6.3 – 40%)

Humalog Mix75/25 is intended only for subcutaneous administration. Humalog Mix75/25 should not be administered intravenously. Dosage regimens of Humalog Mix75/25 will vary among patients and should be determined by the healthcare provider familiar with the patient’s metabolic needs, eating habits, and other lifestyle variables. Humalog has been shown to be equipotent to Regular human insulin on a molar basis. One unit of Humalog has the same glucose–lowering effect as one unit of Regular human insulin, but its effect is more rapid and of shorter duration. Humalog Mix75/25 has a similar glucose–lowering effect as compared with Humulin 70/30 on a unit for unit basis. The quicker glucose–lowering effect of Humalog is related to the more rapid absorption rate of insulin lispro from subcutaneous tissue.

Humalog Mix75/25 starts lowering blood glucose more quickly than Regular human insulin, allowing for convenient dosing immediately before a meal (within 15 minutes). In contrast, mixtures containing Regular human insulin should be given 30 to 60 minutes before a meal.

The rate of insulin absorption and consequently the onset of activity are known to be affected by the site of injection, exercise, and other variables. As with all insulin preparations, the time course of action of Humalog Mix75/25 may vary considerably in different individuals or within the same individual. Patients must be educated to use proper injection techniques.

Humalog Mix75/25 should be inspected visually before use. Humalog Mix75/25 should be used only if it appears uniformly cloudy after mixing. Humalog Mix75/25 should not be used after its expiration date.

HOW SUPPLIED

HOW SUPPLIED

Humalog Mix75/25 [75% insulin lispro protamine suspension and 25% insulin lispro injection, (rDNA origin)] is available in the following package sizes: each presentation containing 100 units insulin lispro per mL (U-100).

10 mL vials | NDC 54868-4381-0 (VL-7511)

STORAGE AND HANDLING

Storage — Humalog Mix75/25 should be stored in a refrigerator [2° to 8°C (36° to 46°F)], but not in the freezer. Do not use Humalog Mix75/25 if it has been frozen. Unrefrigerated [below 30°C (86°F)] vials must be used within 28 days or be discarded, even if they still contain Humalog Mix75/25. Unrefrigerated [below 30°C (86°F)] Pens, and KwikPens must be used within 10 days or be discarded, even if they still contain Humalog Mix75/25. Protect from direct heat and light. See table below:

 | Not In-Use (Unopened) Room Temperature [Below 30°C (86°F)] | Not In-Use (Unopened) Refrigerated | In-Use (Opened) Room Temperature [Below 30°C (86°F)]
10 mL Vial | 28 days | Until expiration date | 28 days, refrigerated/room temperature.
3 mL Pen and KwikPen (prefilled) | 10 days | Until expiration date | 10 days. Do not refrigerate.

Literature revised March 16, 2009

KwikPens manufactured by
Eli Lilly and Company, Indianapolis, IN 46285, USA
Pens manufactured by
Eli Lilly and Company, Indianapolis, IN 46285, USA or
Lilly France, F-67640 Fegersheim, France
Vials manufactured by
Eli Lilly and Company, Indianapolis, IN 46285, USA or
Lilly France, F-67640 Fegersheim, France
for Eli Lilly and Company, Indianapolis, IN 46285, USA

www.humalog.com

Copyright © 2007, 2009, Eli Lilly and Company. All rights reserved.

PV 5551 AMP

Additional bar code labeling applied by:
Physicians Total Care, Inc.
Tulsa, Oklahoma 74146

Patient Information Humalog® (HU-ma-log) Mix75/25TM 75% insulin lispro protamine suspension and 25% insulin lispro injection (rDNA origin)

Important:

Know your insulin. Do not change the type of insulin you use unless told to do so by your healthcare provider. Your insulin dose and the time you take your dose can change with different types of insulin.

Make sure you have the right type and strength of insulin prescribed for you.

Read the Patient Information that comes with Humalog Mix75/25 before you start using it and each time you get a refill. There may be new information. This leaflet does not take the place of talking with your healthcare provider about your diabetes or treatment. Make sure that you know how to manage your diabetes. Ask your healthcare provider if you have questions about managing your diabetes.

What is Humalog Mix75/25?

Humalog Mix75/25 is a mixture of fast-acting and longer-acting man-made insulins. Humalog Mix75/25 is used to control high blood sugar (glucose) in people with diabetes.

Humalog Mix75/25 comes in:

- 10 mL vials (bottles) for use with a syringe
- Prefilled pens

Who should not take Humalog Mix75/25?

Do not take Humalog Mix75/25 if:

- your blood sugar is too low (hypoglycemia). After treating your low blood sugar, follow your healthcare provider's instructions on the use of Humalog Mix75/25.
- you are allergic to anything in Humalog Mix75/25. See the end of this leaflet for a complete list of ingredients in Humalog Mix75/25.

Tell your healthcare provider:

- about all your medical conditions. Medical conditions can affect your insulin needs and your dose of Humalog Mix75/25.
- if you are pregnant or breastfeeding. You and your healthcare provider should talk about the best way to manage your diabetes while you are pregnant or breastfeeding. Humalog Mix75/25 has not been studied in pregnant or nursing women.
- about all the medicines you take, including prescription and non-prescription medicines, vitamins and herbal supplements. Many medicines can affect your blood sugar levels and insulin needs. Your Humalog Mix75/25 dose may need to change if you take other medicines.

Know the medicines you take. Keep a list of your medicines with you to show to all of your healthcare providers.

How should I use Humalog Mix75/25?

Talk to your healthcare provider if you have any questions. Your healthcare provider will tell you the right syringes to use with Humalog Mix75/25 vials. Your healthcare provider should show you how to inject Humalog Mix75/25 before you start using it. Read the User Manual that comes with your Humalog Mix75/25 prefilled pen.

- Use Humalog Mix75/25 exactly as prescribed by your healthcare provider.
- Humalog Mix75/25 starts working faster than other insulins that contain regular human insulin. Inject Humalog Mix75/25 fifteen minutes or less before a meal. If you do not plan to eat within 15 minutes, delay the injection until the correct time (15 minutes before eating).
- Check your blood sugar levels as told by your healthcare provider.
- Mix Humalog Mix75/25 well before each use. For Humalog Mix75/25 in a vial, carefully shake or rotate the vial until completely mixed. For prefilled pens, carefully follow the User Manual for instructions on mixing the pen. Humalog Mix75/25 should be cloudy or milky after mixing well.
- Look at your Humalog Mix75/25 before each injection. If it is not evenly mixed or has solid particles or clumps in it, do not use. Return it to your pharmacy for new Humalog Mix75/25.
- Inject your dose of Humalog Mix75/25 under the skin of your stomach area, upper arm, upper leg, or buttocks. Never inject Humalog Mix75/25 into a muscle or vein.
- Change (rotate) your injection site with each dose.
- Your insulin needs may change because of:
  - illness
  - stress
  - other medicines you take
  - changes in eating
  - physical activity changes
  Follow your healthcare provider's instructions to make changes in your insulin dose.
- Never mix Humalog Mix75/25 in the same syringe with other insulin products.
- Never use Humalog Mix75/25 in an insulin pump.
- Always carry a quick source of sugar to treat low blood sugar, such as glucose tablets, hard candy, or juice.

What are the possible side effects of Humalog Mix75/25?

Low Blood Sugar (Hypoglycemia). Symptoms of low blood sugar include:

- hunger
- dizziness
- feeling shaky or shakiness
- lightheadedness
- sweating
- irritability
- headache
- fast heartbeat
- confusion

Low blood sugar symptoms can happen suddenly. Symptoms of low blood sugar may be different for each person and may change from time to time. Severe low blood sugar can cause seizures and death. Low blood sugar may affect your ability to drive a car or use mechanical equipment, risking injury to yourself or others. Know your symptoms of low blood sugar. Low blood sugar can be treated by drinking juice or regular soda or eating glucose tablets, sugar, or hard candy. Follow your healthcare provider's instructions for treating low blood sugar. Talk to your healthcare provider if low blood sugar is a problem for you.

- Serious allergic reactions (whole body allergic reaction). Severe, life-threatening allergic reactions can happen with insulin. Get medical help right away if you develop a rash over your whole body, have trouble breathing, wheezing, a fast heartbeat, or sweating.
- Reactions at the injection site (local allergic reaction). You may get redness, swelling, and itching at the injection site. If you keep having injection site reactions or they are serious, you need to call your healthcare provider. Do not inject insulin into a skin area that is red, swollen, or itchy.
- Skin thickens or pits at the injection site (lipodystrophy). This can happen if you don't change (rotate) your injection sites enough.

These are not all the side effects from Humalog Mix75/25. Ask your healthcare provider or pharmacist for more information.

How should I store Humalog Mix75/25?

- Store all unopened (unused) Humalog Mix75/25 in the original carton in a refrigerator at 36°F to 46°F (2°C to 8°C). Do not freeze.
- Do not use Humalog Mix75/25 that has been frozen.
- Do not use after the expiration date printed on the carton and label.
- Protect Humalog Mix75/25 from extreme heat, cold or light.

After starting use (open):

- Vials: Keep in the refrigerator or at room temperature below 86°F (30°C) for up to 28 days. Keep open vials away from direct heat or light. Throw away an opened vial 28 days after first use, even if there is insulin left in the vial.
- Prefilled Pens: Do not store a prefilled pen that you are using in the refrigerator. Keep at room temperature below 86°F (30°C) for up to 10 days. Throw away a prefilled pen 10 days after first use, even if there is insulin left in the pen.

General information about Humalog Mix75/25

Use Humalog Mix75/25 only to treat your diabetes. Do not share it with anyone else, even if they also have diabetes. It may harm them.

This leaflet summarized the most important information about Humalog Mix75/25. If you would like more information about Humalog Mix75/25 or diabetes, talk with your healthcare provider. You can ask your healthcare provider or pharmacist for information about Humalog Mix75/25 that is written for health professionals.

For questions you may call 1–800–LillyRx (1–800–545–5979) or visit www.humalog.com.

What are the ingredients in Humalog Mix75/25?

Active ingredients: insulin lispro protamine suspension and insulin lispro.

Inactive ingredients: protamine sulfate, glycerin, dibasic sodium phosphate, metacresol, zinc oxide (zinc ion), phenol and water for injection.

Patient Information issued September 6, 2007

KwikPens manufactured by
Eli Lilly and Company, Indianapolis, IN 46285, USA
Pens manufactured by
Eli Lilly and Company, Indianapolis, IN 46285, USA or
Lilly France, F-67640 Fegersheim, France
Vials manufactured by
Eli Lilly and Company, Indianapolis, IN 46285, USA or
Lilly France, F-67640 Fegersheim, France
for Eli Lilly and Company, Indianapolis, IN 46285, USA

www.humalog.com

Copyright © 2007, Eli Lilly and Company. All rights reserved.

PV 5580 AMP

PATIENT INFORMATION

Humalog® Mix75/25™ KwikPen™
75% insulin lispro protamine suspension and
25% insulin lispro injection (rDNA origin)

Disposable Insulin Delivery Device
User Manual

____________________________________________________________________________________

Introduction

Humalog® Mix75/25™ KwikPen™ (“Pen”) is designed for ease of use. It is a disposable insulin delivery device (“insulin Pen”) containing 3 mL (300 units) of U-100 Humalog® Mix75/25™ [75% insulin lispro protamine suspension and 25% insulin lispro injection (rDNA origin)] insulin. You can inject from 1 to 60 units of Humalog Mix75/25 in one injection. You can dial your dose one unit at a time. If you dial too many units, you can dial backwards to correct the dose without wasting any insulin.

Before using Humalog Mix75/25 KwikPen, read the entire manual completely and follow the directions carefully. If you do not follow these directions completely, you may get too much or too little insulin.

Do not share your Humalog Mix75/25 KwikPen or needles with anyone else. You may give an infection to them or get an infection from them.

DO NOT USE your KwikPen if any part appears broken or damaged. Contact Lilly at 1-800-Lilly-Rx (1-800-545-5979) or your healthcare professional for a replacement Pen. Always carry an extra Pen in case yours is lost or damaged.

This Pen is not recommended for use by the blind or visually impaired persons without the assistance of a person trained in the proper use of the product.

Preparing Humalog Mix75/25 KwikPen

Important Notes

- Read and follow the directions provided in the Patient Information Leaflet.
- Check the label on your Pen before each injection for the expiration date and to make sure you are using the correct type of insulin.
- Your healthcare professional has prescribed the best type of insulin for you. Any changes in insulin therapy should be made only under medical supervision.
- KwikPen is recommended for use with Becton, Dickinson and Company pen needles.
- Be sure the needle is completely attached to the Pen before use.
- Do not share your Pen or needles.
- Keep these directions for future reference.

Frequently Asked Questions about Preparing Humalog Mix75/25 KwikPen

- What should my insulin look like? Humalog Mix75/25 should be cloudy or milky after mixing well. If your Humalog Mix75/25 has solid particles or clumps in it, return it to your pharmacy for a replacement. Be sure to refer to your Patient Information Leaflet for the appearance of your specific insulin.
- Why should I use a new needle for each injection? This will help ensure sterility. If needles are reused, you may get the wrong amount of insulin, a clogged needle or a jammed Pen.
- What should I do if I am not sure how much insulin remains in my cartridge? Hold the Pen with the needle end pointing down. The scale on the clear Cartridge Holder shows an estimate of the number of units remaining. These numbers should NOT be used for measuring an insulin dose.

Priming Humalog Mix75/25 KwikPen

Important Notes

- Prime every time. The Pen must be primed to a stream of insulin before each injection to make sure the Pen is ready to dose.
- If you do not prime, you may get too much or too little insulin.

Frequently Asked Questions about Priming

- Why should I prime my KwikPen before each dose?
  1. Ensures that the Pen is ready to dose.
  2. Confirms that a stream of insulin comes out of the tip of the needle when you push the Dose Knob in.
  3. Removes air that may collect in the needle or insulin cartridge during normal use.
- What should I do if I cannot completely push in the Dose Knob when priming the KwikPen?
  1. Attach a new needle.
  2. Prime the Pen.
- What should I do if I see an air bubble in the cartridge? You need to prime the Pen. Remember, do not store the Pen with the needle attached as this may cause air bubbles to collect in the insulin cartridge. A small air bubble will not affect your dose and you can continue to take your dose as usual.

Injecting Your Dose

Important Notes

- Follow the instructions for sanitary injection technique recommended by your healthcare professional.
- Make sure you receive your complete dose by pushing and holding the dose knob in and count to 5 slowly before removing the needle. If insulin is leaking from the Pen you may not have held it in your skin long enough.
- The Pen will not allow you to dial more than the number of units left in the Pen.
- If your dose is greater than the number of units left in the Pen, you may either inject the amount remaining in your current Pen and then use a new Pen to complete your dose OR inject the full dose with a new Pen.
- Do not attempt to inject your insulin by turning the Dose Knob. You will NOT receive your insulin by turning the Dose Knob. You must PUSH the Dose Knob straight in for the dose to be delivered.
- Do not attempt to change the dose while injecting.
- The directions regarding needle handling are not intended to replace local, healthcare professional or institutional policies.
- Remove the needle after completing each injection.

Frequently Asked Questions about Injecting Your Dose

- Why is it difficult to push the Dose Knob when I try to inject?
  1. Your needle may be clogged. Try attaching a new needle. When you do this you may see insulin come out of the needle. Then prime the Pen.
  2. Pressing the Dose Knob quickly may make the Dose Knob harder to push. Pressing the Dose Knob more slowly may make it easier.
  3. Using a larger diameter needle will make it easier to push the Dose Knob during your injection. See your healthcare professional to determine which needle size is best for you.
  4. If the Dose Knob continues to be difficult to push after following the steps above, try the steps below under “What should I do if my KwikPen is jammed?”.
- What should I do if my KwikPen is jammed? Your Pen may be jammed if it is difficult to inject a dose or dial a dose. To clear the jam:
  1. Attach a new needle. When you do this you may see insulin come out of the needle.
  2. Prime the Pen.
  3. Dial your dose and inject.
  4. If the Dose Knob is still difficult to push, contact Lilly at 1-800-Lilly-Rx (1-800-545-5979).
- Why is insulin leaking from the needle after I finished injecting my dose? You may have removed the needle from your skin too quickly.
  1. Make sure you see a 0 in the Dose Window to confirm you received the complete dose.
  2. For the next dose, push and hold the Dose Knob in and count to 5 slowly before removing the needle.
- What should I do if my dose is dialed and the Dose Knob is accidentally pushed in without a needle attached?
  1. Dial back to zero.
  2. Attach a new needle. When you do this you may see insulin come out of the needle.
  3. Prime the Pen.
  4. Dial your dose and inject.
- What should I do if I dial a wrong dose (too high or too low)? Turn the Dose Knob backward or forward to correct the dose before injecting.
- What should I do if I see insulin leaking from the KwikPen needle while dialing the dose or correcting the dose? Do not inject the dose because you may not get your complete dose. Dial the Pen down to zero and prime the Pen again (see “Priming Humalog Mix75/25 KwikPen” steps 2 B-D). Dial your dose and inject.
- What should I do if my full dose cannot be dialed? The Pen will not allow you to dial a dose greater than the number of insulin units remaining in the cartridge. For example, if you need 31 units and only 25 units remain in the cartridge you will not be able to dial past 25. Do not attempt to dial past this point. You may either:
  1. Inject the partial dose and then inject the remaining dose using a new Pen.
    or
  2. Inject the full dose with a new Pen.
- Why can I not dial the dose to use the small amount of insulin that remains in my cartridge? The Pen is designed to deliver at least 300 units of insulin. The Pen design prevents the cartridge from being completely emptied because the small amount of insulin that remains in the cartridge cannot be delivered.

Storage and Disposal

Important Notes

- Refer to the Patient Information Leaflet for complete insulin storage instructions.
- Pens that have not been used should be stored in a refrigerator but not in a freezer. Do not use a Pen if it has been frozen.
- Do not store the Pen with the needle attached. If the needle remains attached, insulin may leak from the Pen, insulin may dry inside the needle causing the needle to clog, or air bubbles may form inside the cartridge.
- The Pen you are currently using should be kept at room temperature and away from heat and light.
- Keep the Pen out of the reach of children.
- Dispose of used needles in a puncture-resistant container or as directed by your healthcare professional.
- Dispose of used Pens as instructed by your healthcare professional and without the needle attached.

Use the space below to keep track of how long you should use each Pen in the carton. Once you start using a KwikPen it must be thrown out after the number of days listed in your Patient Information Leaflet, even if there is insulin remaining in the Pen. Record the date you start using a Pen, find the number of days that KwikPen should be used in the Patient Information Leaflet and determine the date the Pen should be thrown out. Record the dates in the space provided below.

Example:

Pen 1 - First used on _________ + | Number of days you should = | Throw out on _________
Date | use KwikPen (from Patient | Date
 | Information Leaflet)
Pen 1 - First used on _______ | Throw out on _______
Date | Date
Pen 2 - First used on _______ | Throw out on _______
Date | Date
Pen 3 - First used on _______ | Throw out on _______
Date | Date
Pen 4 - First used on _______ | Throw out on _______
Date | Date
Pen 5 - First used on _______ | Throw out on _______
Date | Date

If you have any questions or problems with your Humalog Mix75/25 KwikPen, contact Lilly at 1-800-Lilly-Rx (1-800-545-5979) or your healthcare professional for assistance.

For more information on Humalog Mix75/25 KwikPen and insulin, please visit our website at www.humalog.com

Humalog® Mix75/25TM and Humalog® Mix75/25TM KwikPenTM are trademarks of Eli Lilly and Company.

Marketed by: Lilly USA, LLC
Indianapolis, IN 46285, USA

Copyright © 2007, 2011, Eli Lilly and Company. All rights reserved.

Humalog Mix75/25 KwikPen meets the current dose accuracy and functional requirements of ISO 11608-1:2000.

Getting Ready
Make sure you have the following items: | □ Humalog® Mix75/25™ KwikPen™ | □ New Pen Needle | □ Alcohol Swab

Pen Parts | KwikPen, and Needle* Assembly *sold separately

Follow these instructions for each injection
1. Preparing Humalog Mix75/25 KwikPen
A. | B. |  | C. | D.
Pull Pen Cap to remove. Be sure to check your insulin for:; - Type - Expiration date - Appearance; Use an alcohol swab to wipe the Rubber Seal on the end of the Cartridge Holder. |  | For Humalog Mix 75/25 insulin: Gently roll the Pen ten times and invert the Pen ten times. The insulin should look evenly mixed. | Remove Paper Tab from Outer Needle Shield. | Push capped needle straight onto the Pen. Screw needle on until secure.

2. Priming Humalog Mix75/25 KwikPen
Caution: If you do not prime before each injection, you may get too much or too little insulin.
A. | B. | C. | D.
Pull off Outer Needle Shield. Do not throw away. Pull off Inner Needle Shield and throw away. | Dial 2 Units by turning the Dose Knob. | Point Pen up. Tap Cartridge Holder to collect air at top. |  | With needle pointing up, push Dose Knob in until it stops and 0 is seen in the Dose Window.
Pull off Outer Needle Shield. Do not throw away. Pull off Inner Needle Shield and throw away. | Dial 2 Units by turning the Dose Knob. | Point Pen up. Tap Cartridge Holder to collect air at top. | Hold Dose Knob in and count to 5 slowly. Priming is complete when a stream of insulin appears from the needle tip and you have counted to 5 slowly. If a stream of insulin does not appear, repeat priming steps 2 B-D up to four times. If the Pen still does not prime, change the needle and repeat the priming steps above. Note: If you do not see a stream of insulin from the tip of the needle and the Dose Knob becomes hard to push, then change the needle and prime the Pen.

3. Injecting Your Dose
A. | B. |  | C. | D.
Turn Dose Knob to the number of units you need to inject. If you dial too many units, you can correct the dose by dialing backwards. Example: 10 units shown. Example: 15 units shown. The even numbers are printed on the dial. The odd numbers, after the number one, are shown as full lines. | Insert needle into skin using injection technique recommended by your healthcare professional. Place your thumb on the Dose Knob and push firmly until the Dose Knob stops. Note: The Pen will not allow you to dial more than the number of units left in the Pen. | To deliver the full dose, hold Dose Knob in and count to 5 slowly. Remove needle from skin. Note: Check to make sure you see 0 in the Dose Window to confirm you received the complete dose. | Carefully replace the Outer Needle Shield. Note: Remove the needle after each injection to keep air out of the cartridge. Do not store the Pen with the needle attached. | Unscrew the capped needle and dispose of as directed by your healthcare professional. Replace Pen Cap.
Turn Dose Knob to the number of units you need to inject. If you dial too many units, you can correct the dose by dialing backwards. Example: 10 units shown. Example: 15 units shown. The even numbers are printed on the dial. The odd numbers, after the number one, are shown as full lines.

Literature revised October 28, 2011

PV 8960 AMP

PACKAGE LABELING

This section contains a representative sample of product package labeling. Product may be manufactured at multiple manufacturing sites. See the How Supplied section for a list of products and associated manufacturing sites.

PACKAGE CARTON – HUMALOG Mix75/25 Vial 10 mL 1ct

NDC 54868-4381-0

10 mL

VL-7511

100 units per mL

Humalog®

Mix75/25TM

75% insulin lispro

protamine suspension

25% insulin lispro injection

(rDNA origin)

For subcutaneous use only.

Rx only

U-100

www.humalog.com